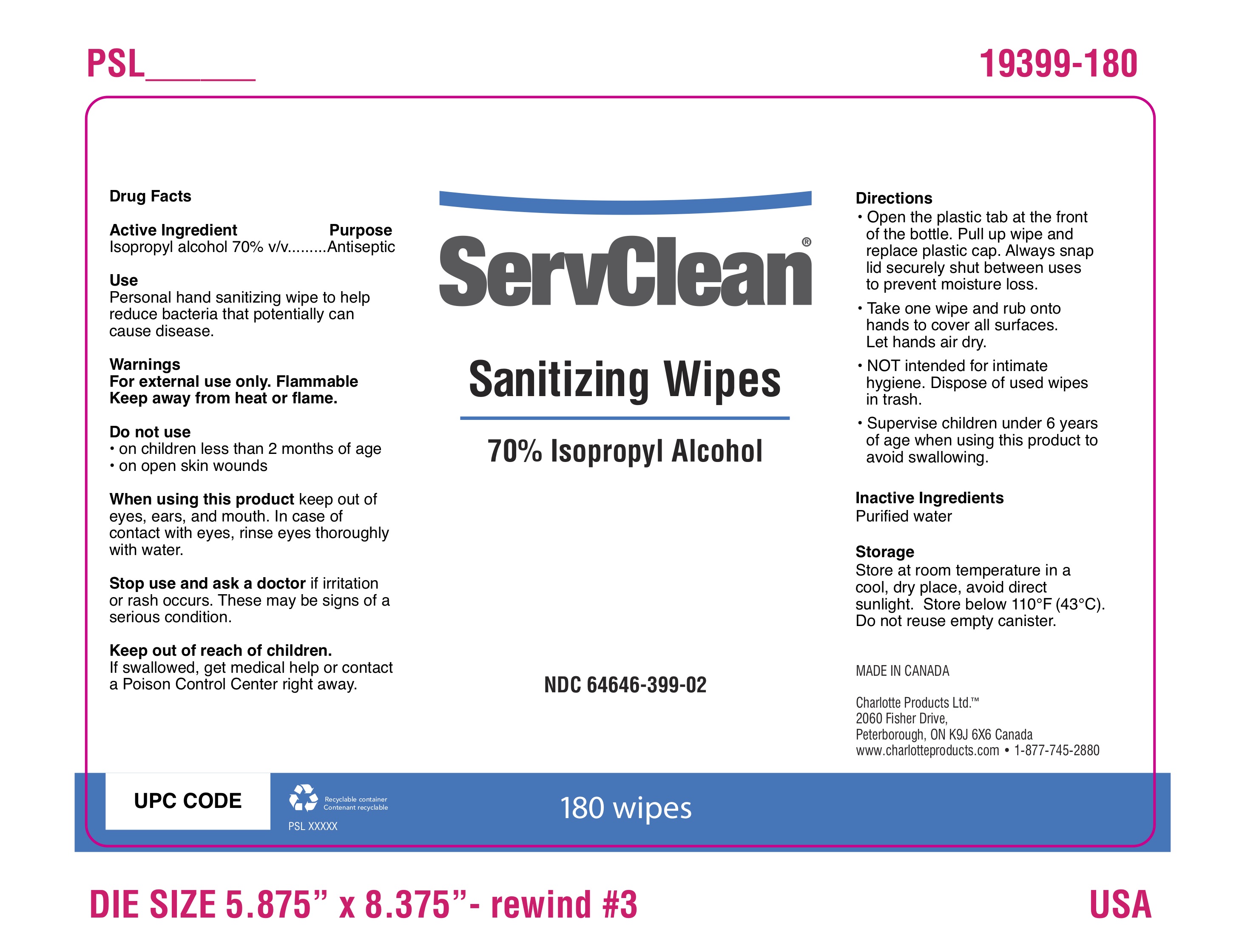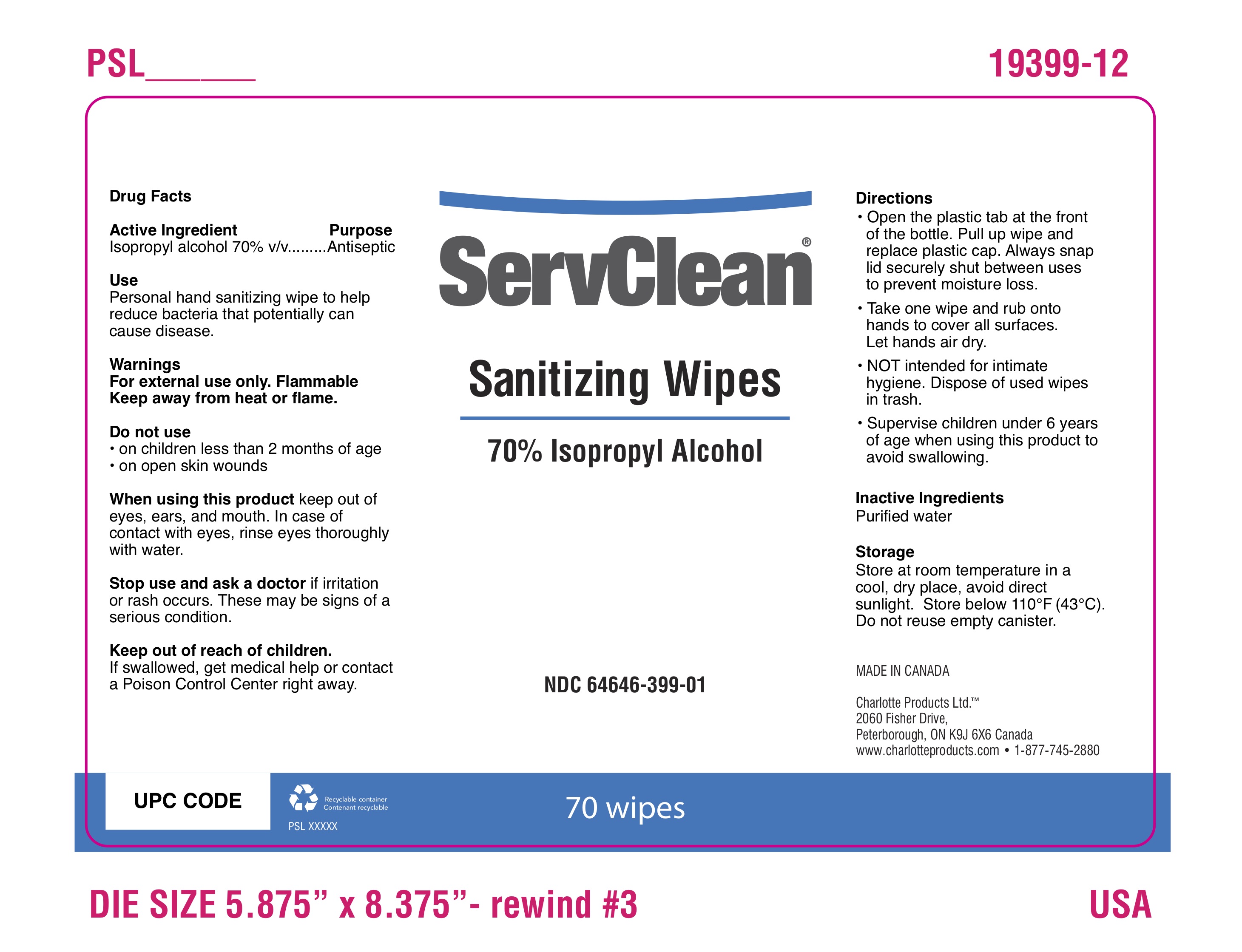 DRUG LABEL: ServClean Sanitizing Wipes
NDC: 64646-399 | Form: CLOTH
Manufacturer: Charlotte Products Ltd.
Category: otc | Type: HUMAN OTC DRUG LABEL
Date: 20210208

ACTIVE INGREDIENTS: ISOPROPYL ALCOHOL 70 mL/100 mL
INACTIVE INGREDIENTS: WATER

ServClean Sanitizing Wipes

This is a hand sanitizer manufactured according to the Temporary Policy for Preparation of Certain Alcohol-Based Hand Sanitizer Products During the Public Health Emergency (CoViD-19); Guidance for Industry.

The hand sanitizer is manufactured using only the following United States Pharmacopoeia (USP) grade ingredients in the preparation of the product (percentage in final product formulation) consistent with World Health Organization (WHO) recommendations:

1. Isopropyl Alcohol (75%, v/v) in an aqueous solution denatured according to Alcohol and Tobacco Tax and Trade Bureau regulations in 27 CFR part 20.
2. Glycerol (1.45% v/v).
3. Hydrogen peroxide (0.125% v/v).
4. Sterile distilled water or boiled cold water.

The firm does not add other active or inactive ingredients. Different or additional ingredients may impact the quality and potency of the product.

Active Ingredient(s)

Isopropyl Alcohol 70% v/v. Purpose: Antiseptic

Purpose

Antiseptic, Hand Sanitizer

Use

Personal hand sanitizing wipe to help reduce bacteria that potentially can cause disease.

Warnings

For external use only. Flammable. Keep away from heat or flame

Do not use

- in children less than 2 months of age
- on open skin wounds

When using this product keep out of eyes, ears, and mouth. In case of contact with eyes, rinse eyes thoroughly with water.
Stop use and ask a doctor if irritation or rash occurs. These may be signs of a serious condition.
Keep out of reach of children. If swallowed, get medical help or contact a Poison Control Center right away.

Stop use and ask a doctor if irritation or rash occurs. These may be signs of a serious condition.

Keep out of reach of children. If swallowed, get medical help or contact a Poison Control Center right away.

Directions

Open the plastic tab at the front of the bottle. Pull up wipe and replace plastic cap. Always snap lid securely shut between uses to prevent moisture loss.

• Take one wipe and rub onto hands to cover all surfaces. Let hands air dry.

• NOT intended for intimate hygiene. Dispose of used wipes in trash.

• Supervise children under 6 years of age when using this product to avoid swallowing.

Storage

Store at room temperature in a cool, dry place, avoid direct sunlight. Store below 110°F (43°C). Do not reuse empty canister.

Inactive ingredients

purified water

Package Label - Principal Display Panel

70 Count NDC: 64646-399-01

180 Count NDC: 64646-399-02